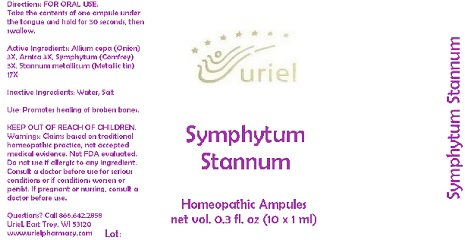 DRUG LABEL: Symphytum Stannum
NDC: 48951-8223 | Form: LIQUID
Manufacturer: Uriel Pharmacy Inc.
Category: homeopathic | Type: HUMAN OTC DRUG LABEL
Date: 20180524

ACTIVE INGREDIENTS: ONION 3 [hp_X]/1 mL; ARNICA MONTANA 3 [hp_X]/1 mL; COMFREY ROOT 3 [hp_X]/1 mL; TIN 17 [hp_X]/1 mL
INACTIVE INGREDIENTS: WATER; SODIUM CHLORIDE

Symphytum Stannum

INDICATIONS AND USAGE

Directions: FOR ORAL USE.

DOSAGE AND ADMINISTRATION

Take the contents of one ampule under the tongue and hold for 30 seconds, then swallow.

ACTIVE INGREDIENT

Active Ingredients: Allium cepa e bulbo 3X, Arnica e pl. tota 3X, Symphytum e rad. 3X, Stannum metallicum 17X

Inactive Ingredients: Water, Salt

PURPOSE

Use: Promotes healing of broken bones.

KEEP OUT OF REACH OF CHILDREN.

WARNINGS

Warnings: Claims based on traditional homeopathic practice, not accepted medical evidence. Not FDA evaluated. Do not use if allergic to any ingredient. Consult a doctor before use for serious conditions or if conditions worsen or persist. If pregnant or nursing, consult a doctor before use.

QUESTIONS

Questions? Call 866.642.2858 Uriel, East Troy, WI 53120 www.urielpharmacy.com